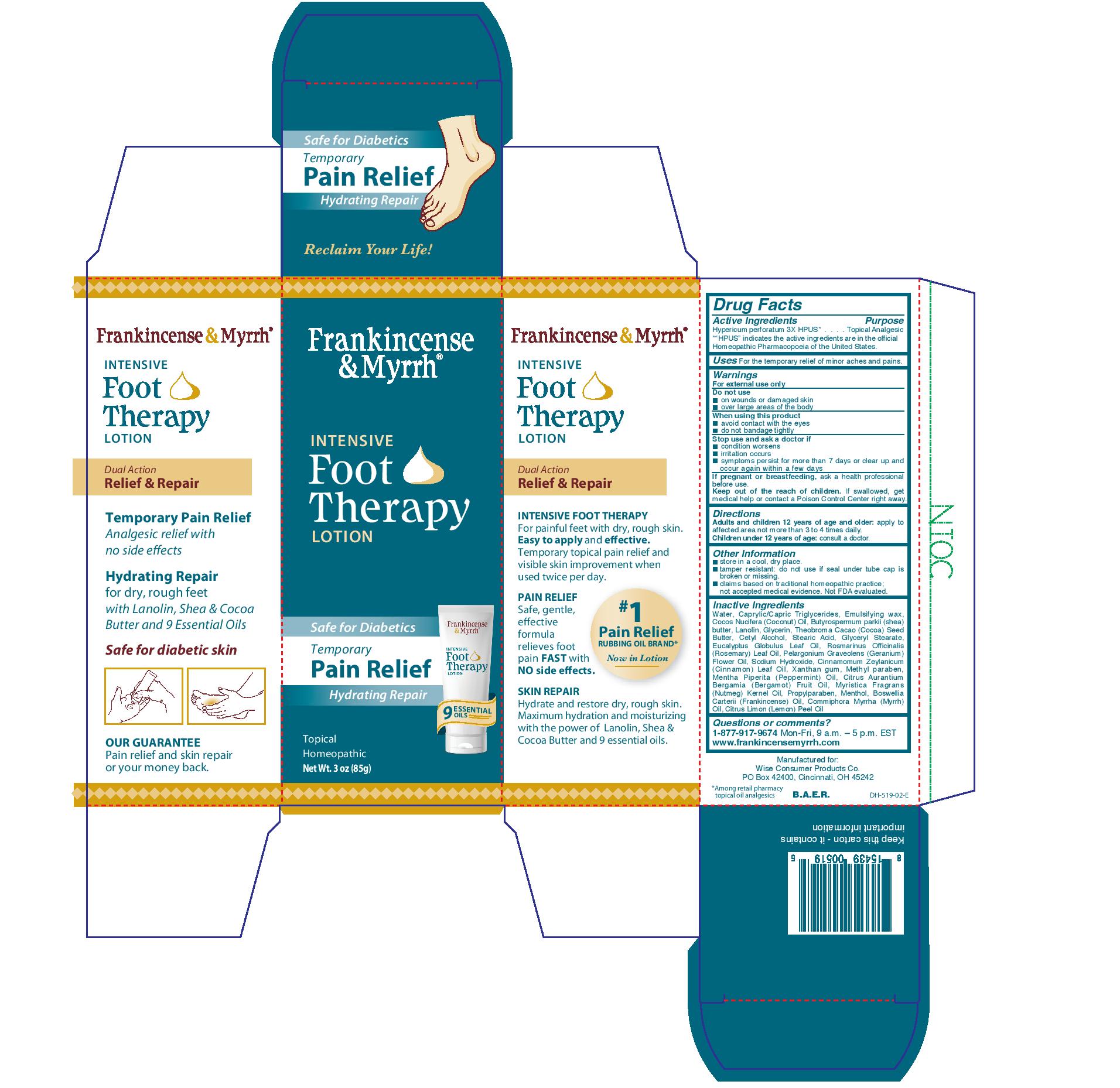 DRUG LABEL: Frankincense and Myrrh
NDC: 42346-519 | Form: LOTION
Manufacturer: Wise Consumer Products Co.
Category: homeopathic | Type: HUMAN OTC DRUG LABEL
Date: 20221227

ACTIVE INGREDIENTS: HYPERICUM PERFORATUM 3 [hp_X]/1 g
INACTIVE INGREDIENTS: EUCALYPTUS OIL; CINNAMON LEAF OIL; XANTHAN GUM; ROSEMARY OIL; SHEA BUTTER; GLYCERIN; CETYL ALCOHOL; MYRRH OIL; COCONUT OIL; GERANIUM OIL, ALGERIAN TYPE; METHYLPARABEN; STEARIC ACID; LANOLIN; SODIUM HYDROXIDE; MENTHOL; WATER; MEDIUM-CHAIN TRIGLYCERIDES; COCOA BUTTER; PEPPERMINT OIL; CITRUS AURANTIUM FRUIT OIL; NUTMEG OIL; PROPYLPARABEN; FRANKINCENSE OIL; LEMON OIL

Active Ingredients

Hypericum perforatum 3X HPUS

"HPUS" indicates the active ingredients are in the official Homeopathic Pharmacopeia of the United States.

Purpose

Hypericum perforatum 3X HPUS.......Topical Analgesic

Uses

For the temporary relief of minor aches and pains.

Warnings

For external use only.

Do not use

- on wounds or damaged skin
- over large areas of the body

When using this product

- avoid contact with the eyes
- do not bandage tightly

Stop use and ask a doctor

- if condition worsens
- if irritaion occurs
- if symptoms persist for more than 7 days or clear up and occur again within a few days

PREGNANCY OR BREAST FEEDING

If pregnant or breastfeeding, ask a health professional before use.

KEEP OUT OF REACH OF CHILDREN

Keep out of the reach of children. If swallowed, get medical help or contact a poison control center right away.

Directions

Adults and children 12 years of age and older: apply to affected area not more than 3 to 4 times daily.

Children under 12 years of age: consult a doctor.

Other Information

- store in a cool, dry place
- tamper resistant: do not use if seal under tube cap is broken or missing.
- claims based on traditional homeopathic practice; not accepted medical evidence. Not FDA evaluated.

Inactive Ingredients

Water, caprylic/capric triglycerides, emulsifying wax, coccos nucifera (coconut) oil, butyrospermum parkii (shea) butter, lanolin, glycerin, theobroma cacao (cocoa) seed butter, cetyl alcohol, stearic acid, glyceryl stearate, eucyalyptus globulus leaf oil, romarinus officinalis (rosemary) leaf oil. pelargonium graveolens (geranium) flower oil, sodium hydroxide, cinnamomum zeylanicum (cinnamon) leaf oil, xanthan gum, methyl paraben, mentha piperita (peppermint) oil, citrus aurantium bergamia (bergamot) fruit oil, myristica fragrans (nutmeg) kernel oil, propylparaben, menthol, boswellia carterii (frankincense) oil, commiphora myrrha (myrrh) oil, citrus limon (lemon) peel oil.

Questions or Comments?

1-877-917-9674 Mon-Fri. 9 a.m. - 5 p.m. EST

www.frankincensemyrrh.com

Manufactured in New Hampshire for:

Wise Consumer Products Co.

PO Box 42400, Cincinnati OH 45242

B.A.E.R

PACKAGE LABEL

Frankincense & Myrrh

Intensive Foot Therapy Lotion

Dual Action

Temporary Pain Relief

Hydrating Repair

Pain Relieving

Topical Lotion

HOMEOPATHIC

Net Wt. 3Oz (85g)